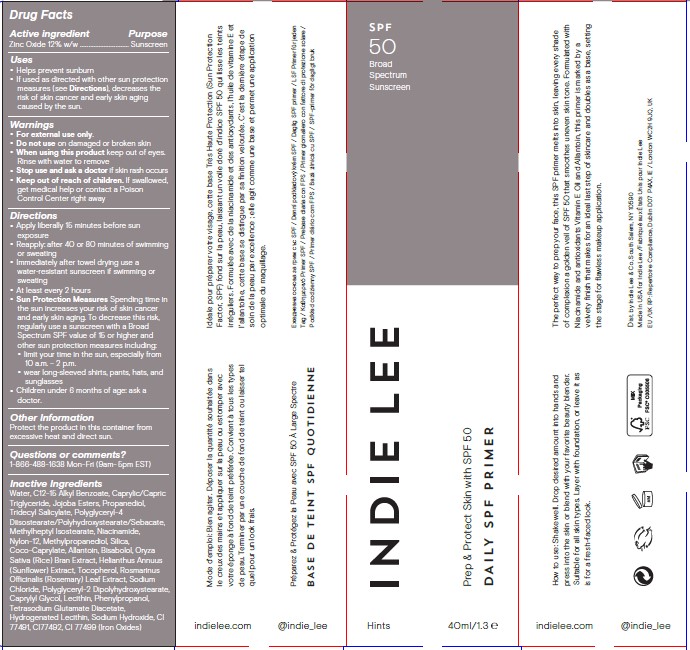 DRUG LABEL: DAILY SPF PRIMER
NDC: 81545-102 | Form: LOTION
Manufacturer: Lee Indie & Co Inc
Category: otc | Type: HUMAN OTC DRUG LABEL
Date: 20230106

ACTIVE INGREDIENTS: ZINC OXIDE 12 g/100 mL
INACTIVE INGREDIENTS: CAPRYLYL GLYCOL; HYDROGENATED SOYBEAN LECITHIN; CAPRYLIC/CAPRIC/LAURIC TRIGLYCERIDE; HYDROGENATED JOJOBA OIL/JOJOBA OIL, RANDOMIZED (IODINE VALUE 64-70); POLYGLYCERYL-4 DIISOSTEARATE/POLYHYDROXYSTEARATE/SEBACATE; PROPANEDIOL; TRIDECYL SALICYLATE; METHYLHEPTYL ISOSTEARATE; SILICON DIOXIDE; NYLON-12; METHYLPROPANEDIOL; COCO-CAPRYLATE; NIACINAMIDE; ALLANTOIN; LEVOMENOL; RICE BRAN; HELIANTHUS ANNUUS WHOLE; TOCOPHEROL; ROSEMARY; SODIUM CHLORIDE; ALKYL (C12-15) BENZOATE; SODIUM HYDROXIDE; FERRIC OXIDE RED; FERROSOFERRIC OXIDE; TETRASODIUM GLUTAMATE DIACETATE; LECITHIN, SUNFLOWER; FERRIC OXIDE YELLOW; PHENYLPROPANOL

INDIE LEE - DAILY SPF PRIMER SPF 50 (81545-102)

ACTIVE INGREDIENT

ZINC OXIDE 12%

PURPOSE

SUNSCREEN

USES

- HELPS PREVENT SUNBURN
- IF USED AS DIRECTED WITH OTHER SUN PROTECTION MEASURES (SEE DIRECTIONS), DECREASES THE RISK OF SKIN CANCER AND EARLY SKIN AGING CAUSED BY THE SUN.

WARNINGS

FOR EXTERNAL USE ONLY.

DO NOT USE ON DAMAGED OR BROKEN SKIN.

WHEN USING THIS PRODUCT KEEP OUT OF EYES. RINSE WITH WATER TO REMOVE.

STOP USE AND CONSULT A PHYSICIAN IF RASH OCCURS.

KEEP OUT OF REACH OF CHILDREN. IF SWALLOWED, GET MEDICAL HELP OR CONTACT A POISON CONTROL CENTER RIGHT AWAY.

DIRECTIONS

- Apply liberally before sun exposure.
- Reapply:
- Use a water-resistant sunscreen if swimming or sweating
- At least every 2 hours
- Sun Protection Measures Spending time in the sun increases your risk of skin cancer and early skin aging. To decrease this risk, regularly use a sunscreen with a Broad Spectrum SPF value of 15 or higher and other sun protection measures including:
- limit your time in the sun, especially from 10 a.m. – 2 p.m.
- wear long-sleeved shirts, pants, hats, and sunglasses
- Children under 6 months of age: ask a doctor.

INACTIVE INGREDIENTS

Water, C12-15 Alkyl Benzoate, Caprylic/Capric Triglyceride, Jojoba Esters, Propanediol, Tridecyl Salicylate, Polyglyceryl-4 Diisostearate/Polyhydroxystearate/Sebacate, Methylheptyl Isostearate, Niacinamide, Nylon-12, Methylpropanediol, Silica, Coco-Caprylate, Allantoin, Bisabolol, Oryza Sativa (Rice) Bran Extract, Helianthus Annuus (Sunflower) Extract, Tocopherol, Rosmarinus Officinalis (Rosemary) Leaf Extract, Sodium Chloride, Polyglyceryl-2 Dipolyhydroxystearate, Caprylyl Glycol, Lecithin, Phenylpropanol, Tetrasodium Glutamate Diacetate, Hydrogenated Lecithin, Sodium Hydroxide, CI 77491, CI77492, CI 77499 (Iron Oxides)

OTHER INFORMATION

Protect this product from excessive heat and direct sun. Store below 90°F (32°C).

QUESTIONS OR COMMENTS?

1 (866) 488-1638 MON-FRI (9 A.M. - 5 P.M. EST)